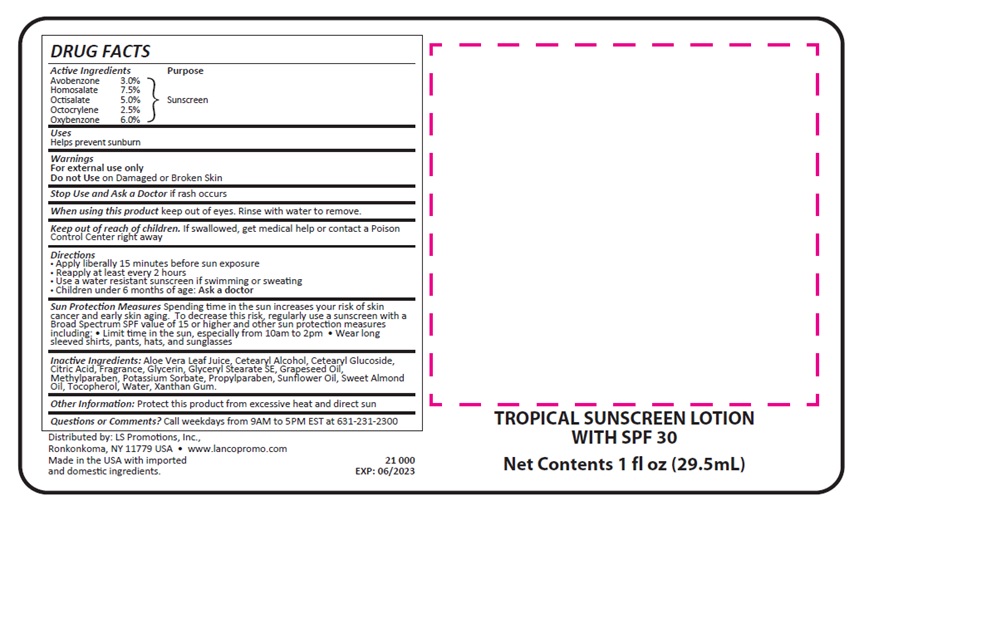 DRUG LABEL: Tropical Sunscreen
NDC: 72449-086 | Form: LOTION
Manufacturer: LS Promotions Inc
Category: otc | Type: HUMAN OTC DRUG LABEL
Date: 20210525

ACTIVE INGREDIENTS: OXYBENZONE 1.8 g/30 mL; HOMOSALATE 2.25 g/30 mL; OCTOCRYLENE 0.75 g/30 mL; OCTISALATE 1.5 g/30 mL; AVOBENZONE 0.9 g/30 mL
INACTIVE INGREDIENTS: TOCOPHEROL; GLYCERIN; GRAPE SEED OIL; CETEARYL GLUCOSIDE; ALOE VERA LEAF; GLYCERYL STEARATE SE; WATER; XANTHAN GUM; POTASSIUM SORBATE; PROPYLPARABEN; SUNFLOWER OIL; ALMOND OIL; CETYL ALCOHOL; ANHYDROUS CITRIC ACID; FRAGRANCE FLORAL ORC0902236; METHYLPARABEN

Tropical Sunscreen Lotion

Drug Facts

Active Ingredients

Avobenzone 3.0%

Homosalate 7.5%

Octisalate 5.0%

Octocrylene 2.5%

Oxybenzone 6.0%

Purpose

Sunscreen

Uses

Helps prevent sunburn

Warnings

For external used only

Do not Use on Damaged or Broken Skin

Stop Use and Ask a Doctor

if rash occurs

When using this product

Keep out of eyes.

Rinse with water to remove.

Keep out of reach of children

If swallowed, get medical help or contact a Poison Control Center right away.

Directions

- Apply liberally 15 minutes before sun exposure
- Reapply at least every 2 hours
- Use a water resistant suncscreen if swimming or sweating
- Children under 6 months of age: Ask a Doctor

Sun Protection Measures

Spending time in the sun increases your risk of skin cancer and early skin aging. To decrease this risk, regularly use a sunscreen with a Broad Spectrum SPF value of 15 or higher and other sun protection measures including: Limit time in the sun, especially from 10am to 2pm. Wear long sleeved shirts, pants, hats, and sunglasses.

Inactive Ingredients

Aloe Vera Leaf Juice, Cetearyl Alcohol, Cetearyl Glucoside,

Citric Acid, Fragrance, Glycerin, Glyceryl Stearate SE, Grapeseed Oil, Methylparaben,

Potassium Sorbate, Propylparaben, Sunflower Oil, Sweet Almond Oil, Tocopherol,

Water, Xanthan Gum.

Other information

Protect this product from excessive heat and direct sun

Questions or Comments?

Call weekdays from 9AM to 5PM EST

at 631-231-2300

Package Label

LK1430 Tropical Sunscreen SPF30